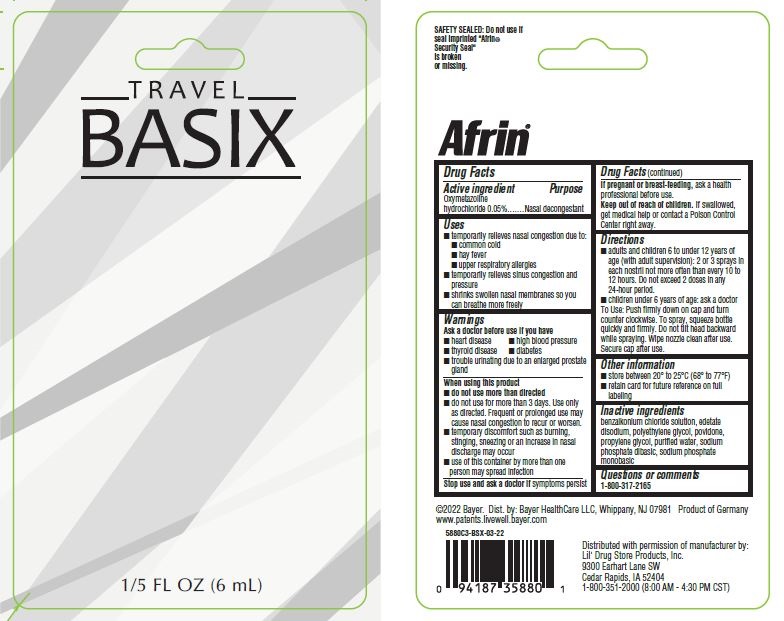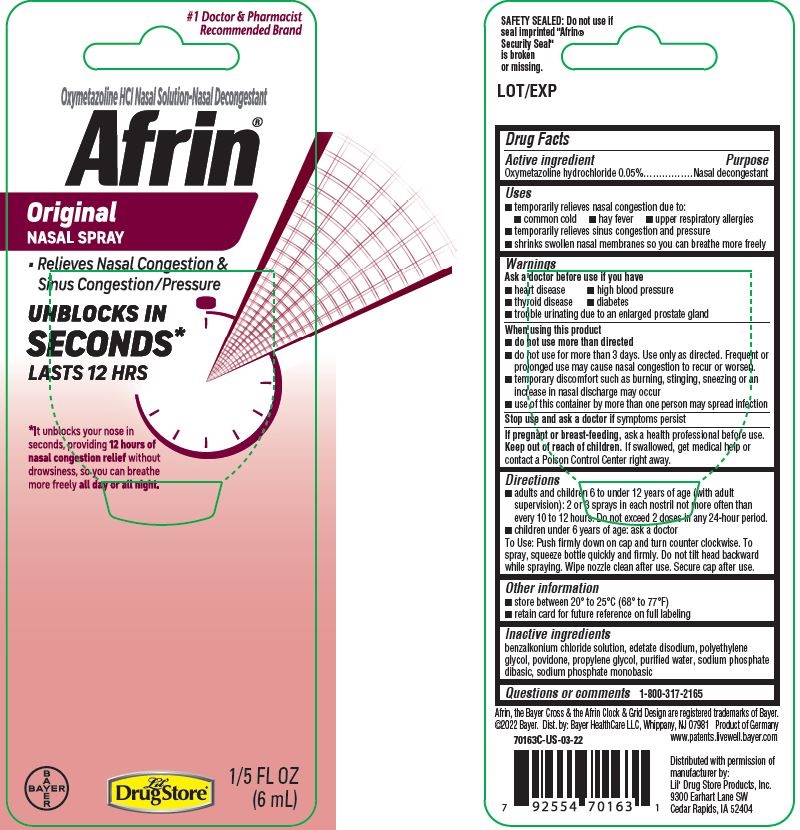 DRUG LABEL: Afrin Original
NDC: 66715-7016 | Form: SPRAY
Manufacturer: Lil' Drug Store Products, Inc.
Category: otc | Type: HUMAN OTC DRUG LABEL
Date: 20241218

ACTIVE INGREDIENTS: OXYMETAZOLINE HYDROCHLORIDE 0.05 g/100 mL
INACTIVE INGREDIENTS: BENZALKONIUM CHLORIDE; EDETATE DISODIUM; POLYETHYLENE GLYCOL, UNSPECIFIED; POVIDONE, UNSPECIFIED; PROPYLENE GLYCOL; WATER; SODIUM PHOSPHATE, DIBASIC, UNSPECIFIED FORM; SODIUM PHOSPHATE, MONOBASIC, UNSPECIFIED FORM

Afrin® Original

Drug Facts

Active ingredient

Oxymetazoline hydrochloride 0.05%

Purpose

Nasal decongestant

Uses

- temporarily relieves nasal congestion due to:
  - common cold
  - hay fever
  - upper respiratory allergies
- temporarily relieves sinus congestion and pressure
- shrinks swollen nasal membranes so you can breathe more freely

Warnings

Ask a doctor before use if you have

- heart disease
- high blood pressure
- diabetes
- thyroid disease
- trouble urinating due to an enlarged prostate gland

When using this product

- do not use more than directed
- do not use for more than 3 days. Use only as directed. Frequent or prolonged use may cause nasal congestion to recur or worsen.
- temporary discomfort such as burning, stinging, sneezing or an increase in nasal discharge may occur
- use of this container by more than one person may spread infection

Stop use and ask a doctor if symptoms persist

PREGNANCY OR BREAST FEEDING

If pregnant or breast-feeding, ask a health professional before use.

Keep out of reach of children. If swallowed, get medical help or contact a Poison Control Center right away.

Directions

- adults and children 6 to under 12 years of age (with adult supervision): 2 or 3 sprays in each nostril not more often than every 10 to 12 hours. Do not exceed 2 doses in any 24-hour period.
- children under 6 years of age: ask a doctor

To spray, squeeze bottle quickly and firmly. Do not tilt head backward while spraying. Wipe nozzle clean after use. Secure cap after use.

Other information

- store between 20° to 25°C (68° to 77°F)
- retain card for future reference on full labeling

Inactive ingredients

benzalkonium chloride solution, edetate disodium, polyethylene glycol, povidone, propylene glycol, purified water, sodium phosphate dibasic, sodium phosphate monobasic

Questions or comments

Call 1-800-317-2165

PDP/PACKAGE - 6 mL Bottle Blister Pack, Lil' Drug Store

#1 Doctor & Pharmacist
Recommended Brand

Oxymetazoline HCl Nasal Solution-Nasal Decongestant

Afrin ® Original

NASAL SPRAY

- Relieves Nasal Congestion &

Sinus Congestion/Pressure

UNBLOCKS IN

SECONDS*

LASTS 12 HRS

*It unblocks your nose in

seconds, providing 12 hours of

nasal congestion relief without

drowsiness, so you can breathe

more freely all day or all night

[Bayer cross]

[Lil' Drug Store logo]

1/5 FL OZ

(6mL)

PDP/Package - BASIX

TRAVEL

BASIX

1/5 FL OZ (6mL)